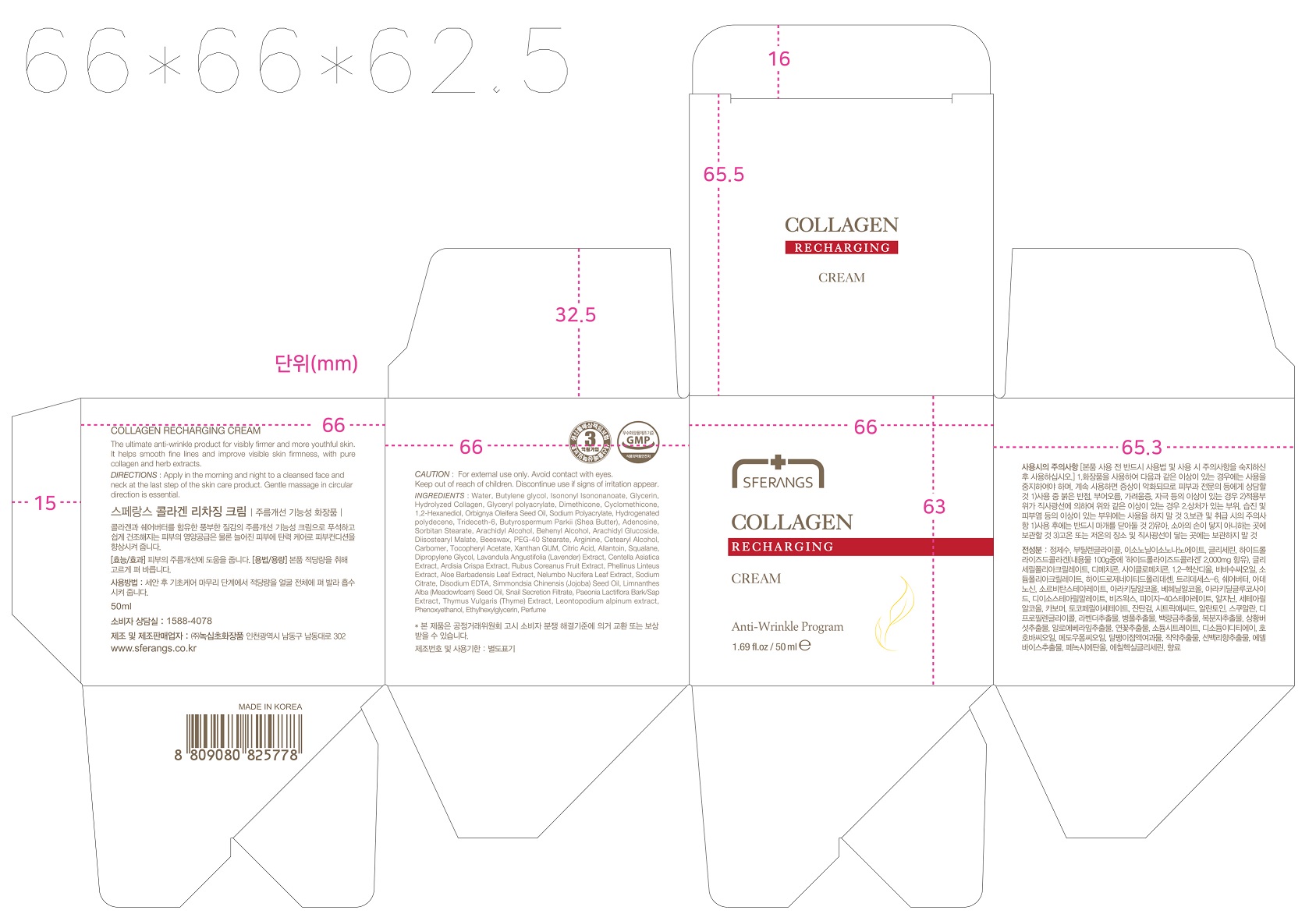 DRUG LABEL: SFERANGS COLLAGEN RECHARGINGCREAM
NDC: 73590-0051 | Form: CREAM
Manufacturer: NOKSIBCHO cosmetic Co., Ltd.
Category: otc | Type: HUMAN OTC DRUG LABEL
Date: 20200430

ACTIVE INGREDIENTS: ADENOSINE 0.04 g/100 mL
INACTIVE INGREDIENTS: WATER

Drug Facts

ACTIVE INGREDIENT

adenosine

INACTIVE INGREDIENT

Water
Butylene glycol
Isononyl Isononanoate
Glycerin
Hydrolyzed Collagen
Glyceryl polyacrylate
1,2-Hexanediol
Orbignya Oleifera Seed Oil
Sodium Polyacrylate
Hydrogenated polydecene
Trideceth-6
Butyrospermum Parkii (Shea Butter)
Sorbitan Stearate
Arachidyl Alcohol
Behenyl Alcohol
Arachidyl Glucoside
Glucose
Diisostearyl Malate
Beeswax
PEG-40 Stearate
Arginine
Cetearyl Alcohol
Carbomer
Tocopheryl Acetate
Xanthan GUM
Citric Acid
Allantoin
Dimethicone
Squalane
Dipropylene Glycol
Lavandula Angustifolia (Lavender) Extract
Propylene Glycol
Centella Asiatica Extract
Phellinus Linteus Extract
Aloe Barbadensis Leaf Extract
Nelumbo Nucifera Leaf Extract
Sodium Citrate
Disodium EDTA
Simmondsia Chinensis (Jojoba) Seed Oil
Limnanthes Alba (Meadowfoam) Seed Oil
Snail Secretion Filtrate
Paeonia Lactiflora Root Extract
Thymus Vulgaris (Thyme) Extract
Leontopodium alpinum extract
Phenoxyethanol
Ethylhexylglycerin
Parfum

PURPOSE

anti-wrinkle

keep out of reach of the children

INDICATIONS AND USAGE

apply proper amount to the skin

WARNINGS

For external use only
When using this product

■ if the following symptoms occurs after use, stop use and consult with a skin specialist

red specks, swelling, itching

■ don’t use on the part where there is injury, eczema, or dermatitis

Keep out of reach of children

■ if swallowed, get medical help or contact a person control center immediately